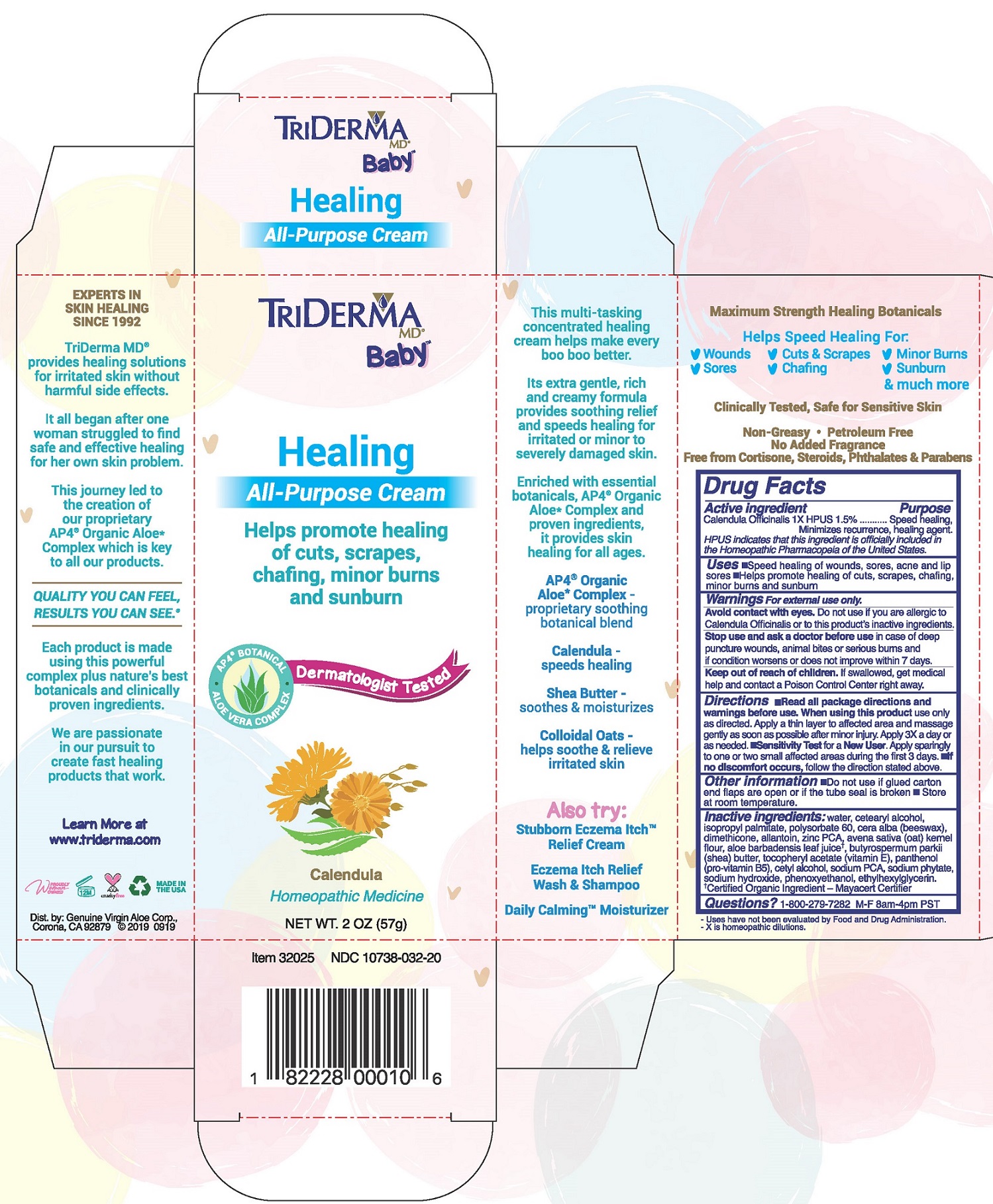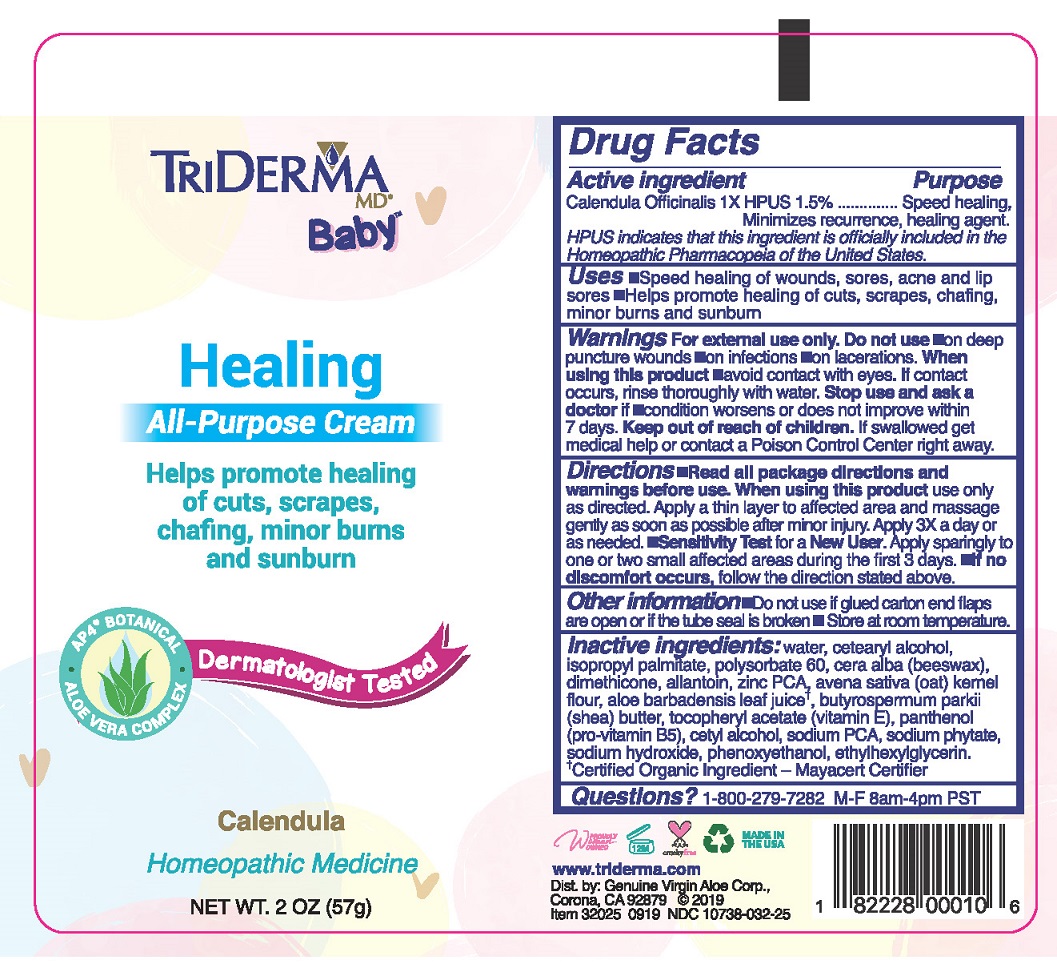 DRUG LABEL: Healing All-Purpose Cream
NDC: 10738-032 | Form: CREAM
Manufacturer: Genuine Virgin Aloe Corporation
Category: homeopathic | Type: HUMAN OTC DRUG LABEL
Date: 20260124

ACTIVE INGREDIENTS: CALENDULA OFFICINALIS FLOWERING TOP 1.5 g/100 g
INACTIVE INGREDIENTS: WATER; CETOSTEARYL ALCOHOL; ISOPROPYL PALMITATE; POLYSORBATE 60; YELLOW WAX; DIMETHICONE; ALLANTOIN; ZINC PIDOLATE; OATMEAL; ALOE VERA LEAF; SHEA BUTTER; .ALPHA.-TOCOPHEROL ACETATE; PANTHENOL; CETYL ALCOHOL; SODIUM PYRROLIDONE CARBOXYLATE; PHYTATE SODIUM; SODIUM HYDROXIDE; PHENOXYETHANOL; ETHYLHEXYLGLYCERIN

Triderma Baby Healing All-Purpose Cream

Active ingredient

Calendula Officinalis 1X HPUS 1.5%

HPUS indicates that this ingredient is officially included in the Homeopathic Pharmacopeia of the United States.

Purpose

Speed healing, Minimizes recurrence, healing agent.

Uses

•speed healing of wounds, sores, acne and lip sores •helps promote healing of cuts, scrapes, chafing, minor burns and sunburn

Warnings

For external use only.

Avoid contact with eyes.

Do not use if you are allergic to Calendula Officinalis or to this product's inactive ingredients.

Stop use and ask a doctor before use in case of deep puncture wounds, animal bites or serious burns and if condition persists for more than 4 days or worsens.

Keep out of reach of children. If swallowed, get medical help and contact a Poison Control Center right away.

Directions

•read all package directions and warnings before use. When using this product use only as directed. Apply a thin layer to affected area and massage gently as soon as possible after minor injury. Apply 3X a day or as needed •Sensitivity Test for a New User. Apply sparingly to one or two small affected areas during the first 3 days. •if no discomfort occurs, follow the direction stated above.

Other information

Do not use if glued carton end flaps are open or if the tube seal is broken. •store at room temperature.

Inactive ingredients

water, cetearyl alcohol, isopropyl palmitate, polysorbate 60, cera alba(beeswax), dimethicone, allantoin, zinc PCA, avena sativa (oat) kernel flour, aloe barbadensis leaf juice, butyrospermum parkii (shea) butter, tocopheryl acetate (vitamin E), panthenol (pro-vitamin B5), cetyl alcohol, sodium PCA, sodium phytate, sodium hydroxide, phenoxyethanol, ethylhexylglycerin.

Questions?

1-800-279-7282 M-F 8am-4pm PST

Packaging

Triderma MD Baby

Healing all-Purpose Cream

Helps promote healing of cuts, scrapes, chafing, minor burns, and sunburn

Dermatologist Tested
Calendula
Homeopathic Medicine

NET WT. 2 oz (57 g)